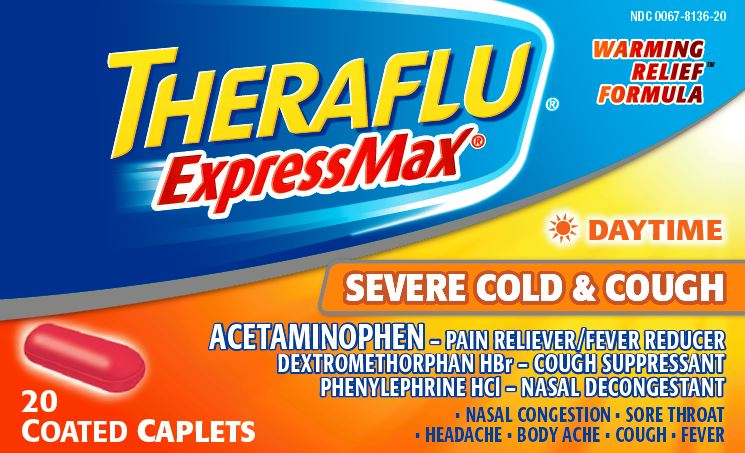 DRUG LABEL: Theraflu ExpressMax

NDC: 0067-8136 | Form: TABLET, FILM COATED
Manufacturer: Haleon US Holdings LLC
Category: otc | Type: HUMAN OTC DRUG LABEL
Date: 20240307

ACTIVE INGREDIENTS: ACETAMINOPHEN 325 mg/1 1; DEXTROMETHORPHAN HYDROBROMIDE 10 mg/1 1; PHENYLEPHRINE HYDROCHLORIDE 5 mg/1 1
INACTIVE INGREDIENTS: BENZOIC ACID; CROSCARMELLOSE SODIUM; ALCOHOL; FERRIC OXIDE YELLOW; HYPROMELLOSE, UNSPECIFIED; MAGNESIUM STEARATE; MALTODEXTRIN; MICROCRYSTALLINE CELLULOSE; POLYETHYLENE GLYCOL, UNSPECIFIED; POLYSORBATE 60; POLYSORBATE 80; POVIDONE, UNSPECIFIED; STARCH, CORN; PROPYLENE GLYCOL; SILICON DIOXIDE; STEARIC ACID; SUCRALOSE; TITANIUM DIOXIDE

Drug Facts

Active ingredient

Acetaminophen 325 mg

Dextromethorphan HBr 10 mg

Phenylephrine HCl 5 mg

Purpose

Pain reliever/fever reducer

Cough suppressant

Nasal decongestant

Uses

- temporarily relieves these symptoms due to a cold:
  - minor aches and pains
  - minor sore throat pain
  - headache
  - nasal and sinus congestion
  - cough due to minor throat and bronchial irritation
- temporarily reduces fever

Warnings

Liver warning:This product contains acetaminophen. Severe lever damage may occur if you take

- more than 4,000 mg of acetaminophen in 24 hours
- with other drugs containing acetaminophen
- 3 or more alcoholic drinks every day while using this product

Allergy alert:Acetaminophen may cause severe skin reactions. Symptoms may include:

- skin reddening
- blisters
- rash

If a skin reaction occurs, stop use and seek medical help right away.

Sore throat warning:If sore throat is severe, persists for more than 2 days, is accompanied or followed by fever, headache, rash, nausea, or vomiting consult a doctor promptly.

Do not use

- in a child under 12 years of age
- if you are allergic to acetaminophen
- with any other drug containing acetaminophen (prescription or nonprescription). If you are not sure whether a drug contains acetaminophen, ask a doctor or pharmacist.
- if you are now taking a prescription monoamine oxidase inhibitor (MAOI) (certain drugs for depression, psychiatric, or emotional conditions, or Parkinson’s disease), or for 2 weeks after stopping the MAOI drug. If you do not know if your prescription drug contains an MAOI, ask a doctor or pharmacist before taking this product.

Ask a doctor before use if you have

- liver disease
- heart disease
- high blood pressure
- thyroid disease
- diabetes
- trouble urinating due to an enlarged prostate gland
- cough that occurs with too much phlegm (mucus)
- cough that lasts or is chronic such as occurs with smoking, asthma or emphysema

Ask a doctor or pharmacist before use if you are

- taking the blood thinning drug warfarin

When using this product

- do not exceed recommended dosage

Stop use and ask a doctor if

- nervousness, dizziness, or sleeplessness occurs
- fever gets worse or lasts more than 3 days
- redness or swelling is present
- new symptoms occur
- pain, cough or nasal congestion gets worse or lasts more than 7 days
- cough comes back or occurs with rash or headache that lasts. These could be signs of a serious condition.

If pregnant or breast-feeding,

ask a health professional before use.

Keep out of reach of children.

In case of overdose, get medical help or contact a Poison Control Center right away. Prompt medical attention is critical for adults as well as for children even if you do not notice any signs or symptoms.

Directions

- do not use more than directed
- adults and children 12 years of age and over: take 2 caplets every 4 hours, while symptoms persist. Do not take more than 10 caplets in 24 hours unless directed by a doctor.
- children under 12 years of age: do not use

Other information

- store at controlled room temperature 20°-25°C (68°-77°F)

Inactive ingredients

benzoic acid, carmine, croscarmellose sodium, ethanol, ferric oxide yellow, flavors, hypromellose, magnesium stearate, maltodextrin, microcrystalline cellulose, polyethylene glycol, polysorbate 60, polysorbate 80, povidone, pregelatinized starch, propylene glycol, silicon dioxide, stearic acid, sucralose, titanium dioxide

Questions or Comments?

call 1-800-452-0051

Principal Display Panel

NDC 0067-8136-20

Theraflu®ExpressMax®

DAYTIME

SEVERE COLD & COUGH

WARMING RELIEF™ FORMULA

ACETAMINOPHEN – PAIN RELIEVER/FEVER REDUCER

DEXTROMETHORPHAN HBr – COUGH SUPPRESSANT

PEHNYLEPHRINE HCl – NASAL DECONGESTANT

- NASAL CONGESTION • SORE THROAT
- HEADACHE • BODY ACHE • COUGH • FEVER

20 COATED CAPLETS

READ ALL WARNINGS AND DIRECTIONS ON CARTON BEFORE USE. KEEP CARTON FOR REFERENCE. DO NOT DISCARD.

PARENTS:

Learn about teen medicine abuse

www.StopMedicineAbuse.org

*Maximum Strength per 4 hour dose.

TAMPER EVIDENT FEATURE:

THERAFLU ®EXPRESSMAX ®CAPLETS ARE SEALED IN BLISTER PACKETS. USE ONLY IF THE INDIVIDUAL SEAL IS UNBROKEN.

Distributed by: GSK Consumer Healthcare,Warren, NJ 07059

Trademarks are owned by or licensed to the GSK group of companies.

©2016 GSK group of companies or its licensor. All rights reserved.

www.theraflu.com

62000000010595